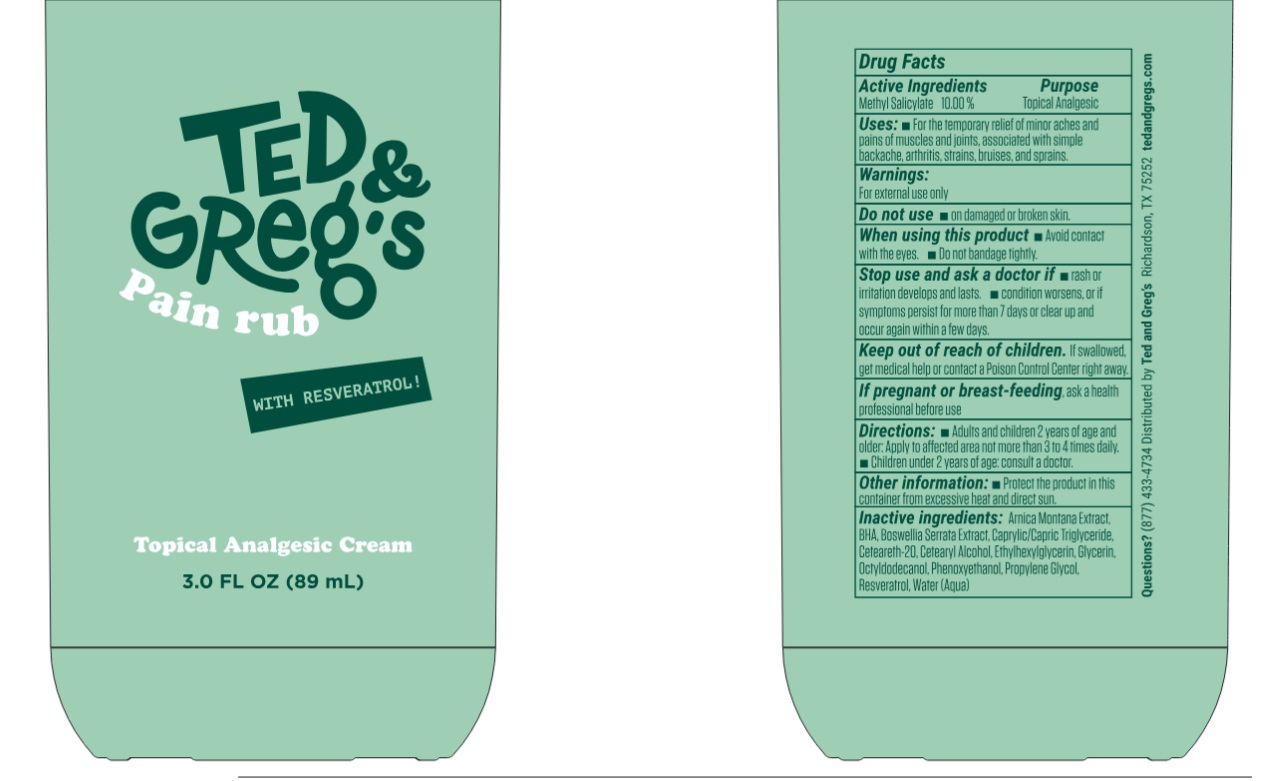 DRUG LABEL: Ted and Gregs Pain Rub with Resveratrol Topical Analgesic
NDC: 87163-920 | Form: CREAM
Manufacturer: Ted and Greg's Inc.
Category: otc | Type: HUMAN OTC DRUG LABEL
Date: 20251229

ACTIVE INGREDIENTS: METHYL SALICYLATE 100 mg/1 mL
INACTIVE INGREDIENTS: ARNICA MONTANA WHOLE; BUTYLATED HYDROXYANISOLE; INDIAN FRANKINCENSE; MEDIUM-CHAIN TRIGLYCERIDES; POLYOXYL 20 CETOSTEARYL ETHER; CETOSTEARYL ALCOHOL; ETHYLHEXYLGLYCERIN; GLYCERIN; OCTYLDODECANOL; PHENOXYETHANOL; PROPYLENE GLYCOL; RESVERATROL; WATER

Ted & Greg's Pain Rub with Resveratrol Topical Analgesic Cream

Active Ingredients

Methyl Salicylate 10.00%

Purpose

Topical Analgesic

Uses:

- For the temporary relief of minor aches and pains of muscles and joints, associated with simple backache, arthritis, strains, bruises, and sprains.

Warnings:

For external use only

Do not use

- on damaged or broken skin.

When using this product

- Avoid contact with the eyes.
- Do not bandage tightly.

Stop use and ask a doctor if

- rash or irritation develops and lasts.
- condition worsens, or if symptoms persist for more than 7 days or clear up and occur again within a few days.

Keep out of reach of children.

If swallowed, get medical help or contact a Poison Control Center right away.

If pregnant or breast-feeding,

ask a health professional before use

Directions:

- Adults and children 2 years of age and older: Apply to affected area not more than 3 to 4 times daily.
- Children under 2 years of age: consult a doctor.

Other information:

- Protect the product in this container from excessive heat and direct sun.

Inactive ingredients:

Arnica Montana Extract, BHA, Boswellia Serrata Extract, Caprylic/Capric Triglyceride, Ceteareth-20, Cetearyl Alcohol, Ethylhexylglycerin, Glycerin, Octyldodecanol, Phenoxyethanol, Propylene Glycol, Resveratrol, Water (Aqua)